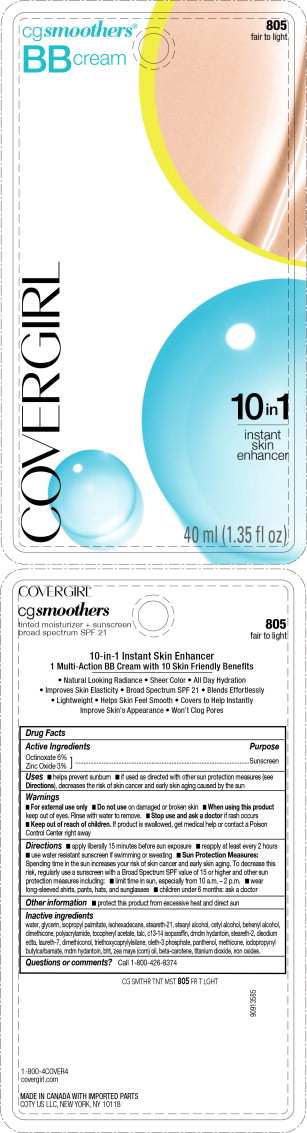 DRUG LABEL: Covergirl cgsmoothers BB Tinted Moisturizer
NDC: 22700-001 | Form: CREAM
Manufacturer: Noxell Corporation
Category: otc | Type: HUMAN OTC DRUG LABEL
Date: 20241119

ACTIVE INGREDIENTS: OCTINOXATE 6 g/100 mL; ZINC OXIDE 3 g/100 mL
INACTIVE INGREDIENTS: WATER; GLYCERIN; ISOHEXADECANE; ISOPROPYL PALMITATE; OLETH-3 PHOSPHATE; .ALPHA.-TOCOPHEROL ACETATE; IODOPROPYNYL BUTYLCARBAMATE; DMDM HYDANTOIN; STEARETH-21; STEARETH-2; STEARYL ALCOHOL; DOCOSANOL; TALC; DIMETHICONE; PANTHENOL; C13-14 ISOPARAFFIN; EDETATE DISODIUM; BUTYLATED HYDROXYTOLUENE; .BETA.-CAROTENE; METHICONE (20 CST); CETYL ALCOHOL; LAURETH-7; TITANIUM DIOXIDE; FERRIC OXIDE RED

Covergirl® cgsmoothers BB Tinted Moisturizer
Broad Spectrum SPF 21

Drug Facts

Active Ingredients

Octinoxate 6%
Zinc Oxide 3%

Purpose

Sunscreen

Uses

- helps prevent sunburn
- if used as directed with other sun protection measures (see Directions), decreases the risk of skin cancer and early skin aging caused by the sun

Warnings

- For external use only

- Do not use on damaged or broken skin

- When using this product keep out of eyes. Rinse with water to remove.

- Stop use and ask a doctor if rash occurs

- Keep out of reach of children. If product is swallowed, get medical help or contact a Poison Control Center right away

Directions

- apply liberally 15 minutes before sun exposure
- reapply at least every 2 hours
- use water resistant sunscreen if swimming or sweating
- Sun Protection Measures: Spending time in the sun increases your risk of skin cancer and early skin aging. To decrease this risk, regularly use a sunscreen with a Broad Spectrum SPF value of 15 or higher and other sun protection measures including:
  - limit time in sun, especially from 10 a.m. – 2 p.m.
  - wear long-sleeved shirts, pants, hats, and sunglasses
- children under 6 months: ask a doctor

Other information

- protect this product from excessive heat and direct sun

Inactive ingredients

water, glycerin, isohexadecane, isopropyl palmitate, oleth-3 phosphate, sucrose polycottonseedate, tocopheryl acetate, iodopropynyl butylcarbamate, dmdm hydantoin, steareth-21, steareth-2, stearyl alcohol, behenyl alcohol, talc, polyacrylamide, dimethicone, dimethiconol, panthenol, c13-14 isoparaffin, disodium edta, bht, beta-carotene, methicone, cetyl alcohol, laureth-7, titanium dioxide, iron oxides.

Questions or comments?

Call 1-800-426-8374

PRINCIPAL DISPLAY PANEL - 40 ml Tube Blister Pack Label

cg smoothers®
BB cream

805
fair to light

COVERGIRL

10in1

instant
skin
enhancer

40 ml (1.35 fl oz)